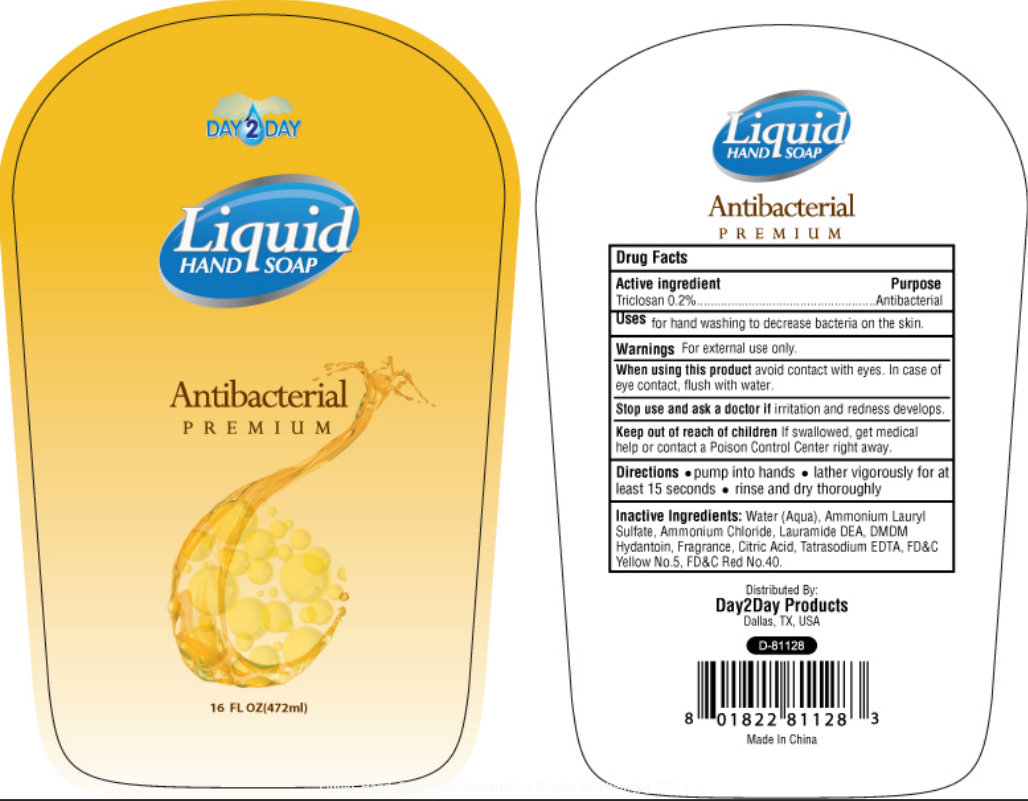 DRUG LABEL: Hand Antibacterial Premium
NDC: 76088-200 | Form: SOAP
Manufacturer: King Import Warehouse
Category: otc | Type: HUMAN OTC DRUG LABEL
Date: 20110330

ACTIVE INGREDIENTS: TRICLOSAN 0.2 mL/100 mL
INACTIVE INGREDIENTS: WATER; AMMONIUM LAURYL SULFATE; LAURIC DIETHANOLAMIDE; DMDM HYDANTOIN; CITRIC ACID MONOHYDRATE; EDETATE SODIUM; FD&C YELLOW NO. 5; FD&C RED NO. 40

DAY2DAY LIQUID HAND SOAP ANTIBACTERIAL PREMIUM

Active ingredient

Triclosan 0.2%

Purpose

Antibacterial

INDICATIONS AND USAGE

Uses for hand washing to decrease bacteria on the skin.

Warnings For external use only.

When using this product avoid contact with eyes. In case of eye contact, flush with water.

Stop use and ask doctor if irritation and redness develops.

Keep out of reach of children if swallowed, get medical help or contact a Poison Control Center right away.

Directions

- pump into hands
- lather vigorously for at least 15 seconds
- rinse and dry thoroughly

INACTIVE INGREDIENT

Inactive Ingredients: Water (Aqua), Ammonium Lauryl Sulfate, Ammonium Chloride, Lauramide DEA, DMDM Hydantoin, Fragrance, Citric Acid, Tatrasodium EDTA, FD and C Yellow No. 5, FD and C Red No. 40.

PACKAGE LABEL

DAY2DAY

Liquid

Hand Soap

Antibacterial

Premium

16 FL OZ (472ml)